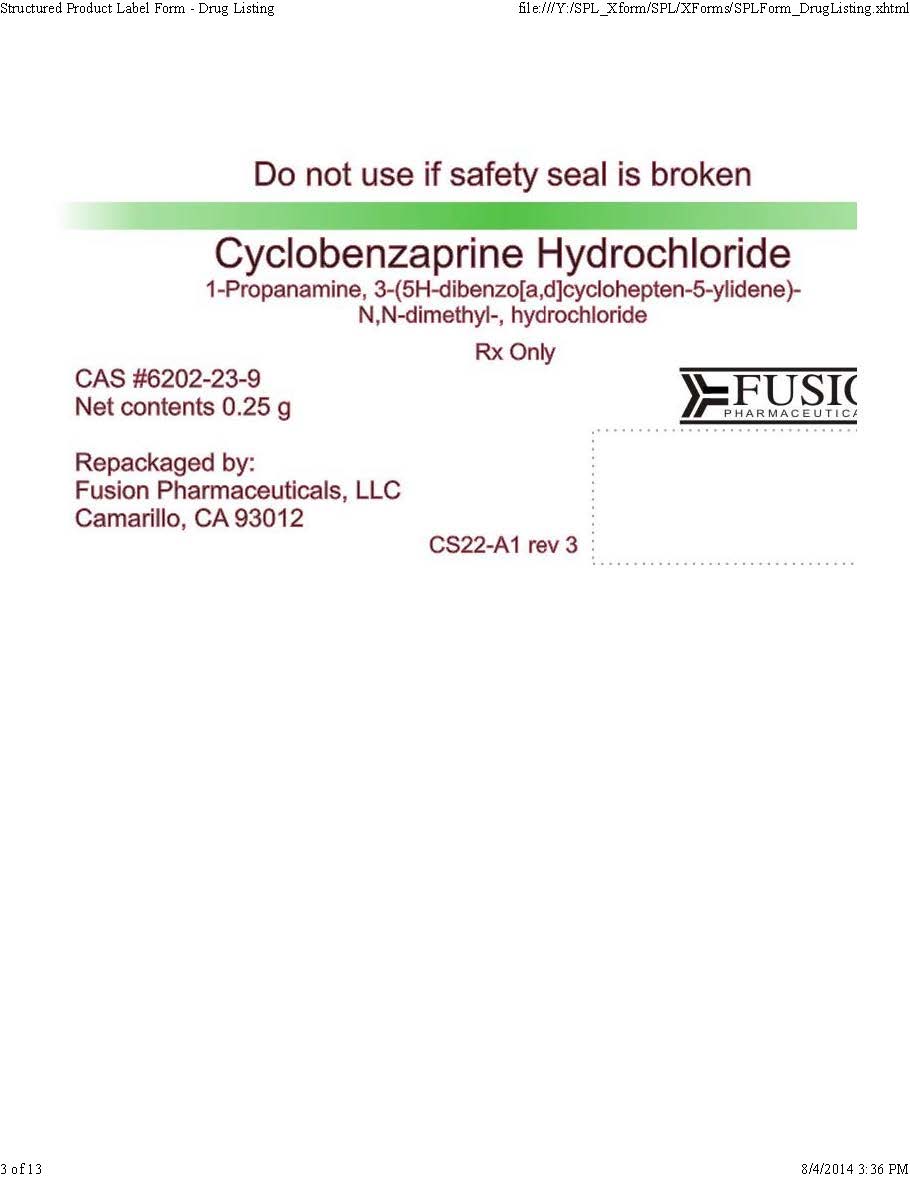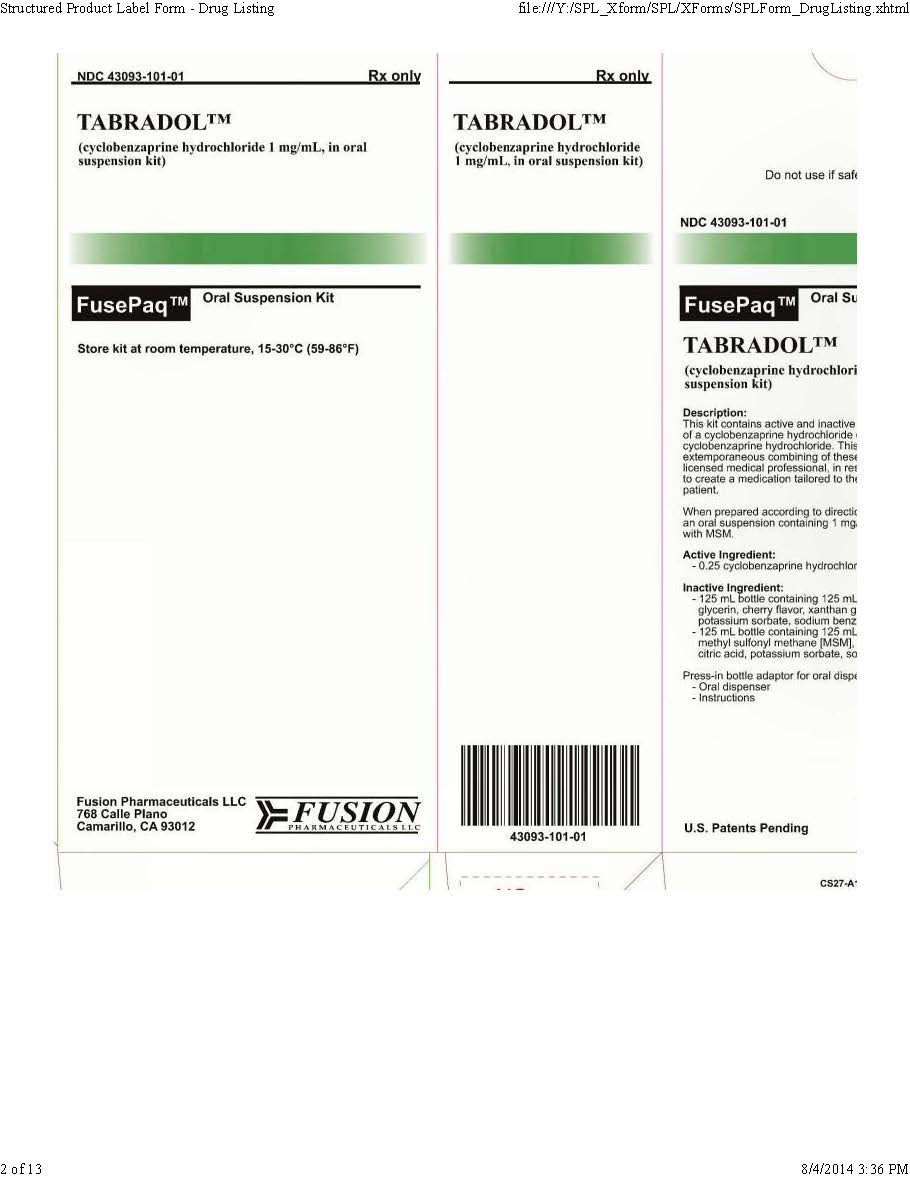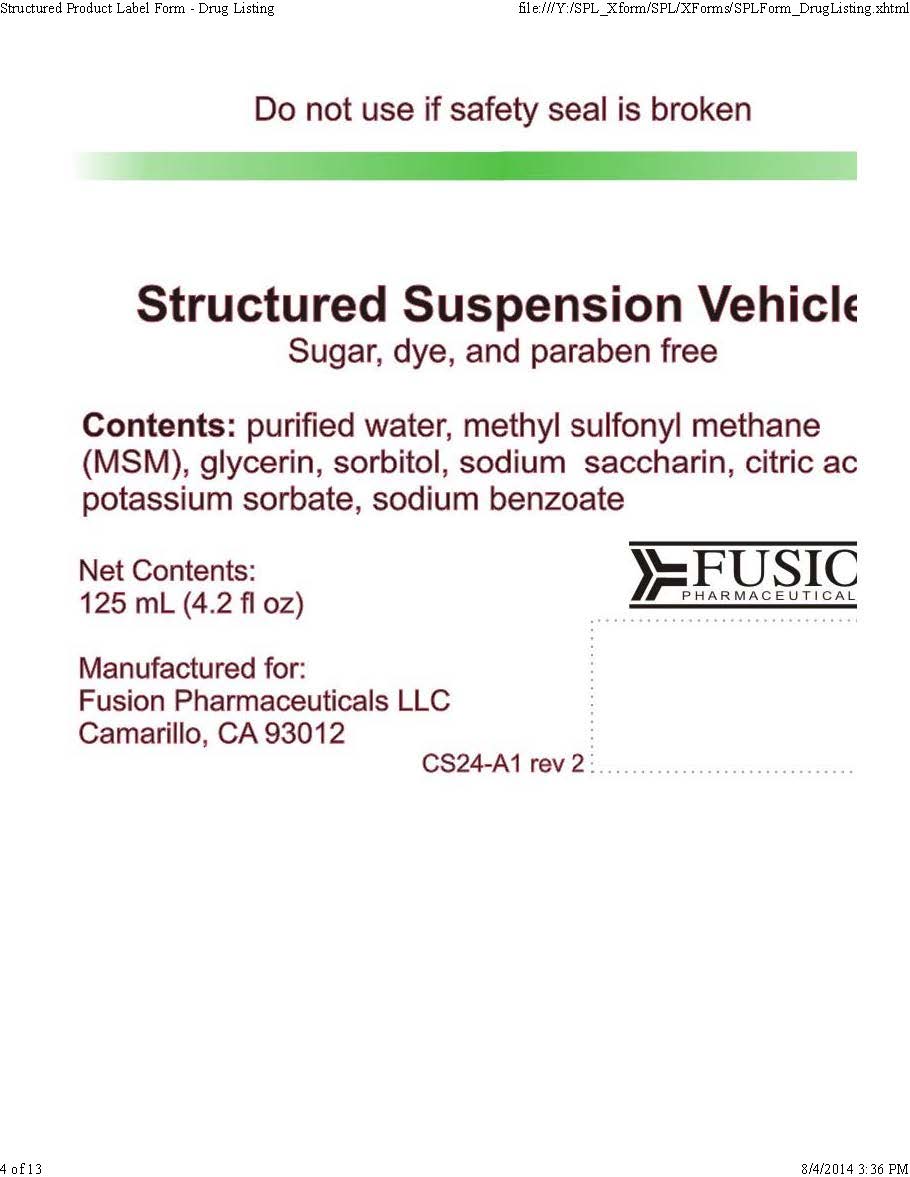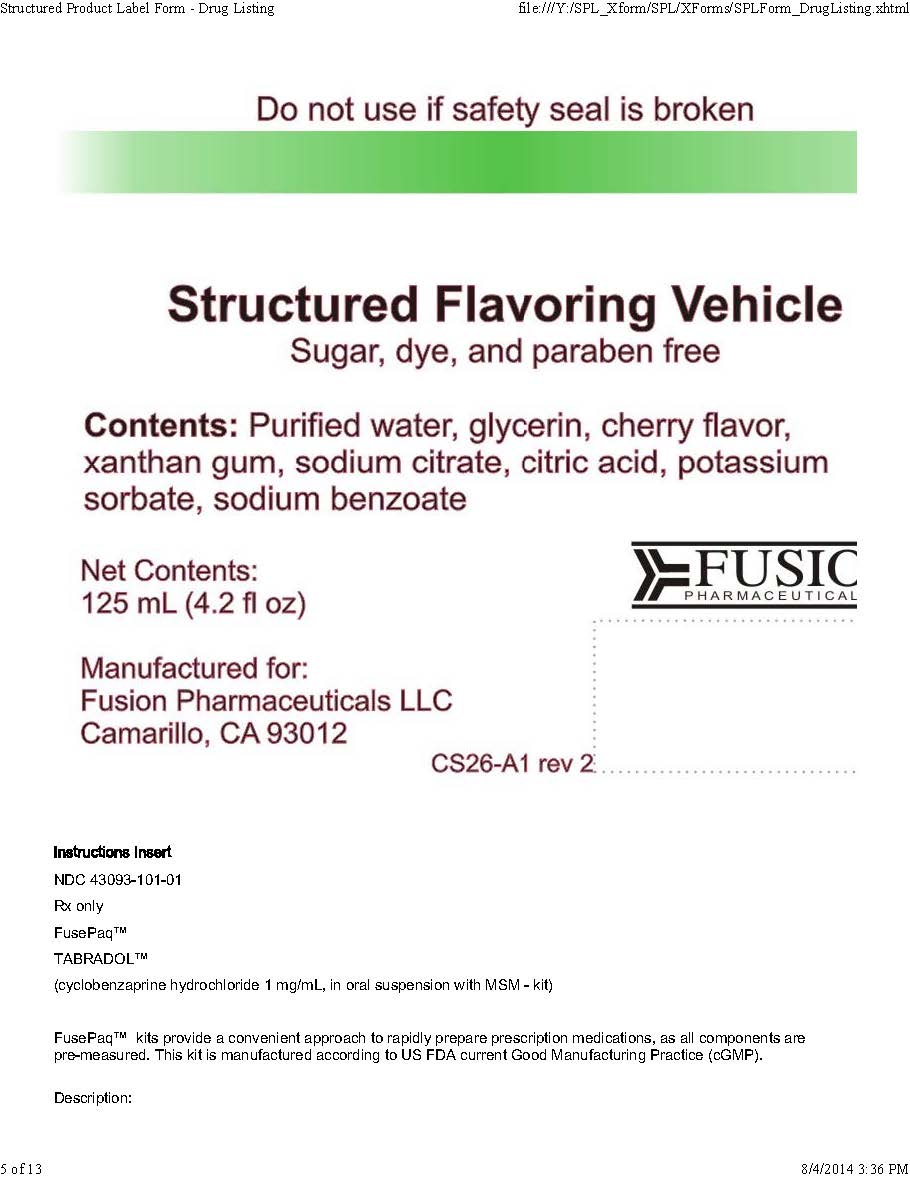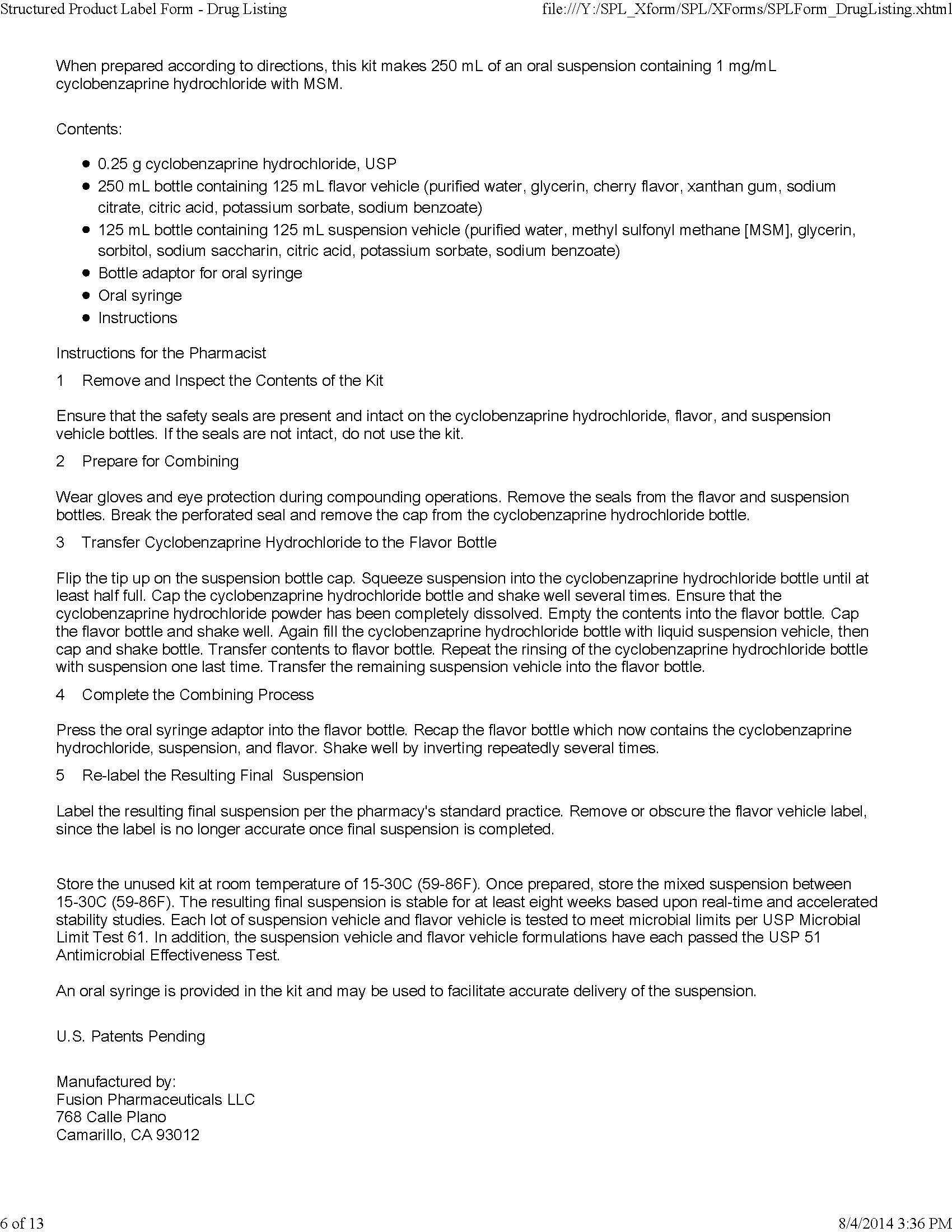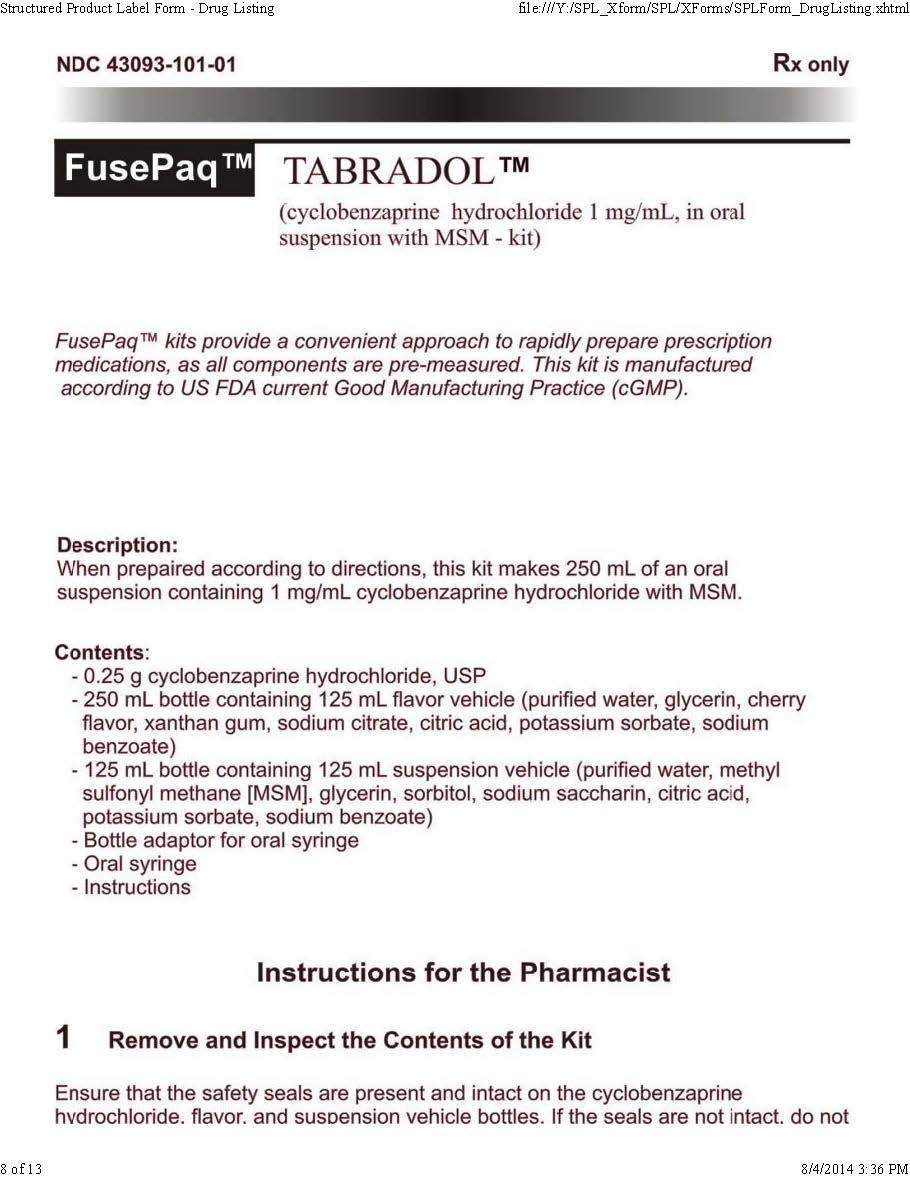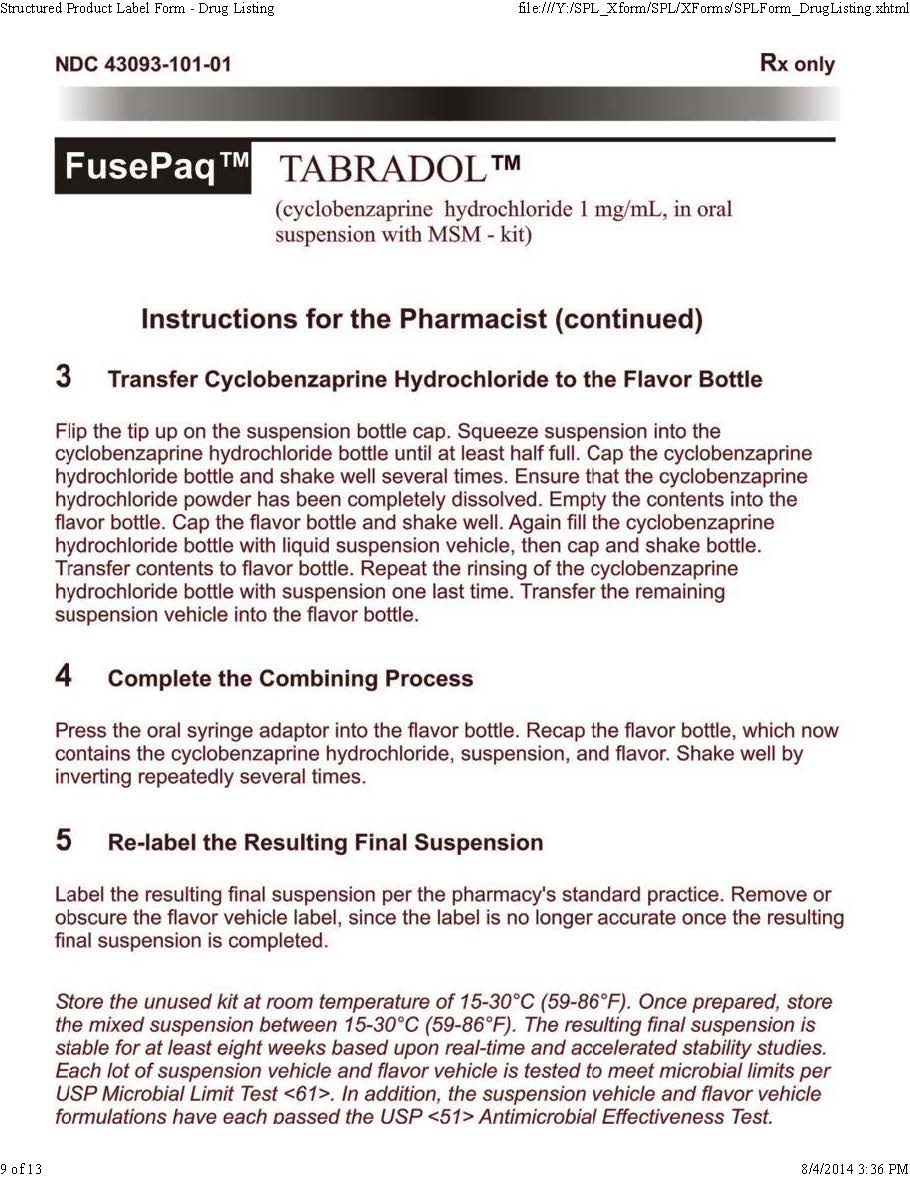 DRUG LABEL: Tabradol
NDC: 43093-101 | Form: KIT | Route: ORAL
Manufacturer: Fusion Pharmaceuticals LLC
Category: prescription | Type: HUMAN PRESCRIPTION DRUG LABEL
Date: 20160107

ACTIVE INGREDIENTS: CYCLOBENZAPRINE HYDROCHLORIDE 0.28 g/0.28 g
INACTIVE INGREDIENTS: WATER; GLYCERIN; SORBITOL; SACCHARIN SODIUM; POTASSIUM SORBATE; SODIUM BENZOATE; DIMETHYL SULFONE; CITRIC ACID MONOHYDRATE; WATER; GLYCERIN; CHERRY; XANTHAN GUM; SODIUM CITRATE; POTASSIUM SORBATE; SODIUM BENZOATE; CITRIC ACID MONOHYDRATE

TABRADOL